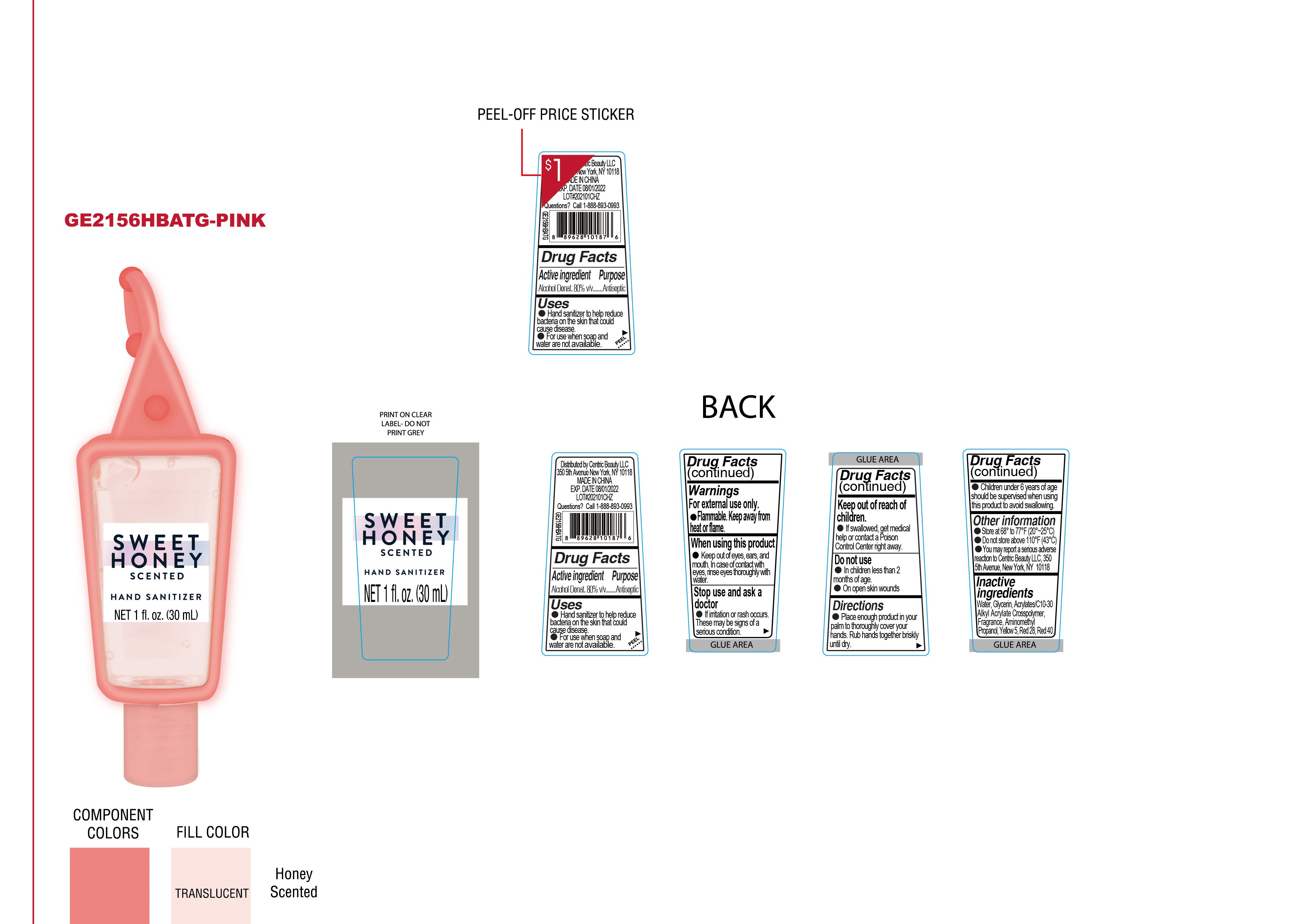 DRUG LABEL: Sweet Honey Hand Sanitizer
NDC: 51522-015 | Form: GEL
Manufacturer: Gold Orient International Limited
Category: otc | Type: HUMAN OTC DRUG LABEL
Date: 20200617

ACTIVE INGREDIENTS: ALCOHOL 80 mL/100 mL
INACTIVE INGREDIENTS: FD&C RED NO. 40; GLYCERIN; WATER; D&C RED NO. 28; CARBOMER COPOLYMER TYPE A (ALLYL PENTAERYTHRITOL CROSSLINKED); AMINOMETHYLPROPANOL; FD&C YELLOW NO. 5

Active Ingredient(s)

Alcohol Denat 80% v/v.

Purpose

Antiseptic

Use

Hand Sanitizer to help reduce bacteria that could cause disease. For use when soap and water are not available.

Warnings

For external use only. Flammable. Keep away from heat or flame

Do not use

- in children less than 2 months of age
- on open skin wounds

When using this product keep out of eyes, ears, and mouth. In case of contact with eyes, rinse eyes thoroughly with water.
Stop use and ask a doctor if irritation or rash occurs. These may be signs of a serious condition.
Keep out of reach of children. If swallowed, get medical help or contact a Poison Control Center right away.

Stop use and ask a doctor if irritation or rash occurs. These may be signs of a serious condition.

Keep out of reach of children. If swallowed, get medical help or contact a Poison Control Center right away.

Directions

- Place enough product on hands to cover all surfaces. Rub hands together until dry.
- children under 6 years of age should be supervised when using this product to avoid swallowing.

Other information

- Store between 68 to 77F(20-25C)
- Do not store above 100F (43C)
- You may report a serious adverse reaction to Centric Beauty LLC, 350 5th Avenue, New York, NY 10118

Inactive ingredients

Water, Glycerin, Acrylates/C10-30 Alkyl Acrylate Crosspolymer, Aminomethyl Propanol, Yellow 5, Red 28, Red 40